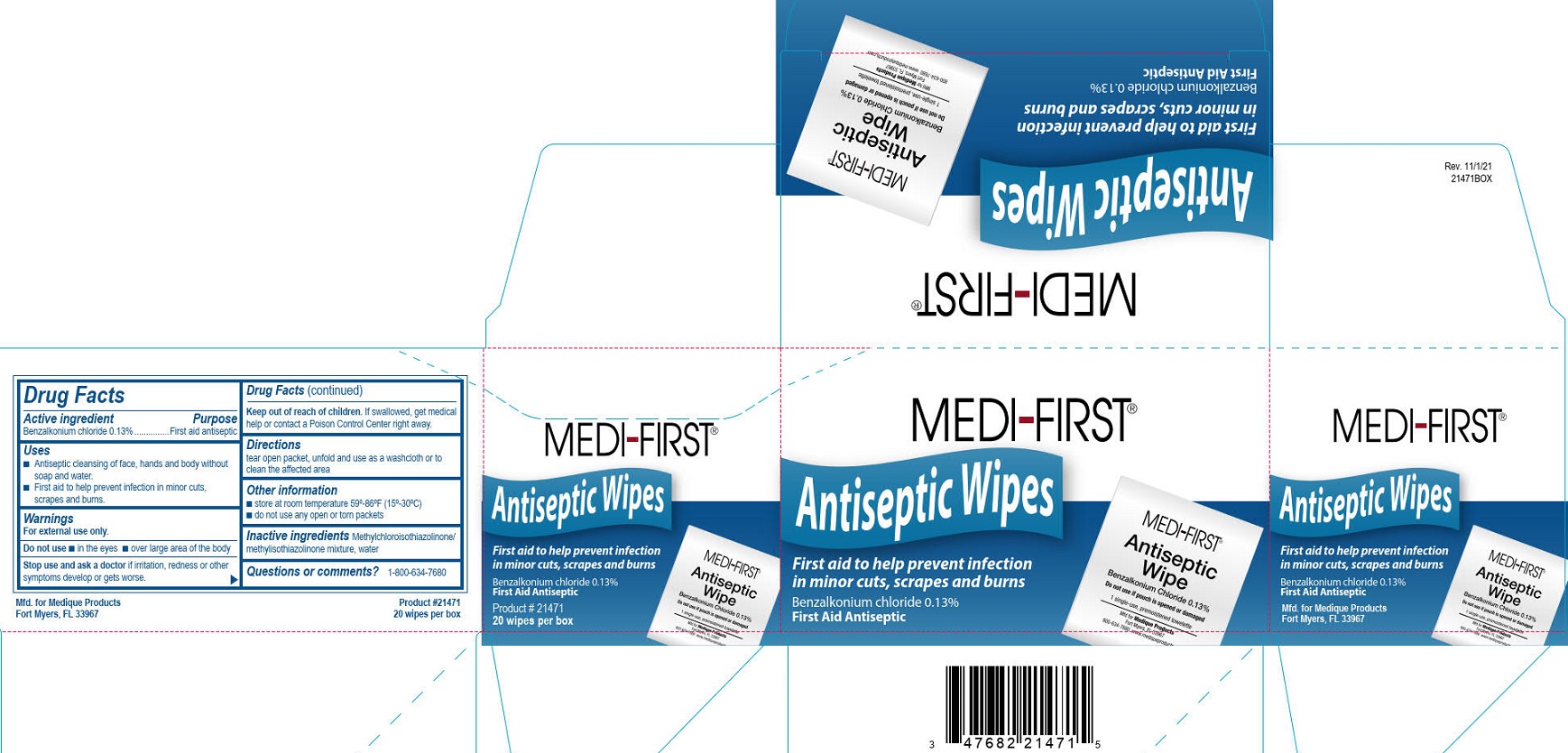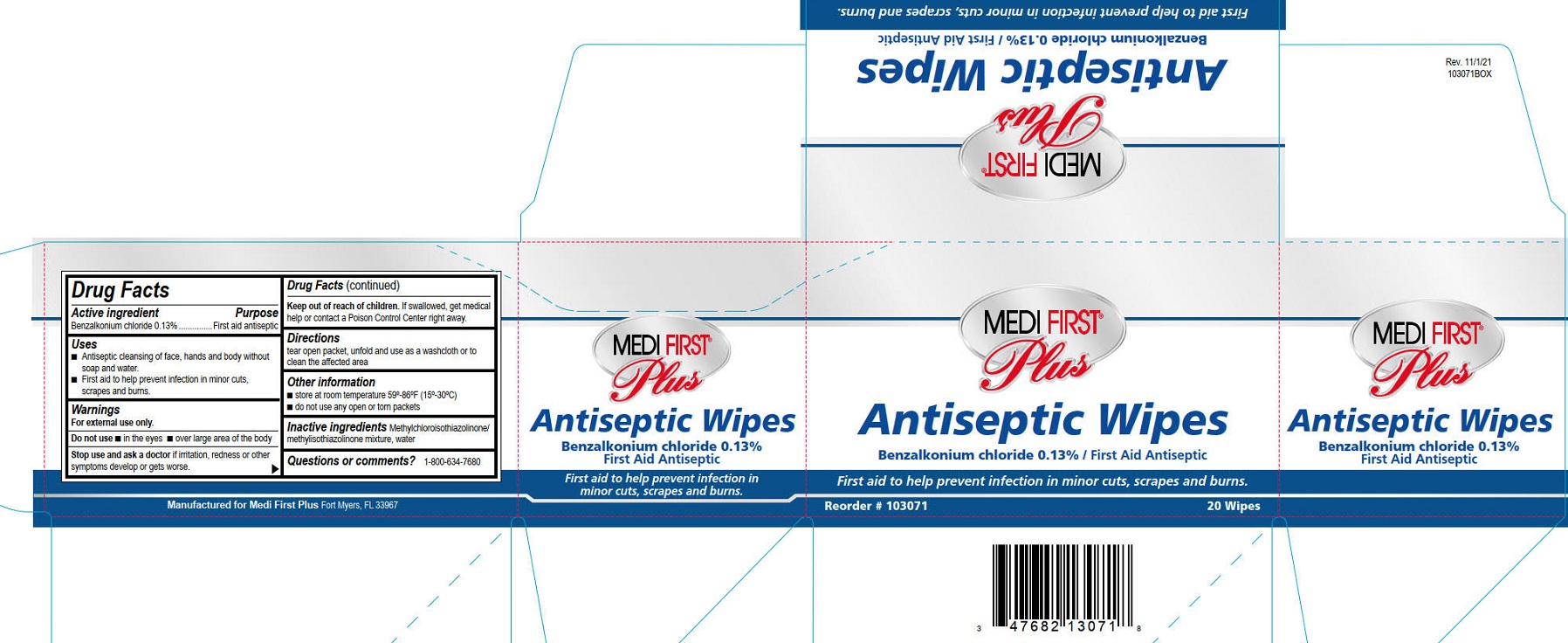 DRUG LABEL: Medi-First Antiseptic Wipes
NDC: 47682-122 | Form: CLOTH
Manufacturer: Unifirst First Aid Corporation
Category: otc | Type: HUMAN OTC DRUG LABEL
Date: 20250908

ACTIVE INGREDIENTS: BENZALKONIUM CHLORIDE 1.3 mg/1 1
INACTIVE INGREDIENTS: METHYLCHLOROISOTHIAZOLINONE/METHYLISOTHIAZOLINONE MIXTURE; WATER

Medique Antiseptic Wipes

Drug Facts

Active ingredient

Benzalkonium chloride 0.13%

Purpose

First aid antiseptic

Uses

- Antiseptic cleansing of face, hands and body without soap and water.
- First aid to help prevent infection in minor cuts, scrapes and burns.

Warnings

For external use only.

Do not use

- in the eyes
- over large area of the body

Stop use and ask a doctor if irritation, redness or other symptoms develop or gets worse.

Keep out of reach of children. If swallowed, get medical help or contact a Poison Control Center right away.

Directions

tear open packet, unfold and use as a washcloth or to clean the affected area

Other information

- store at room temperature 59º-86ºF (15º-30ºC)
- do not use any open or torn packets

INACTIVE INGREDIENT

Inactive ingredients Methylchloroisothiazolinone/methylisothiazolinone mixture, water

PACKAGE LABEL

Medi-First®

Antiseptic Wipes

First aid to help prevent infection in minor cuts, scrapes and burns

Benzalkonium chloride 0.13%

First Aid Antiseptic

PACKAGE LABEL

Medi-First® Plus

Antiseptic Wipes

Benzalkonium chloride 0.13% / First Aid Antiseptic

First aid to help prevent infection in mminor cuts, scrapes and burns.

Reorder # 103071

20 wipes